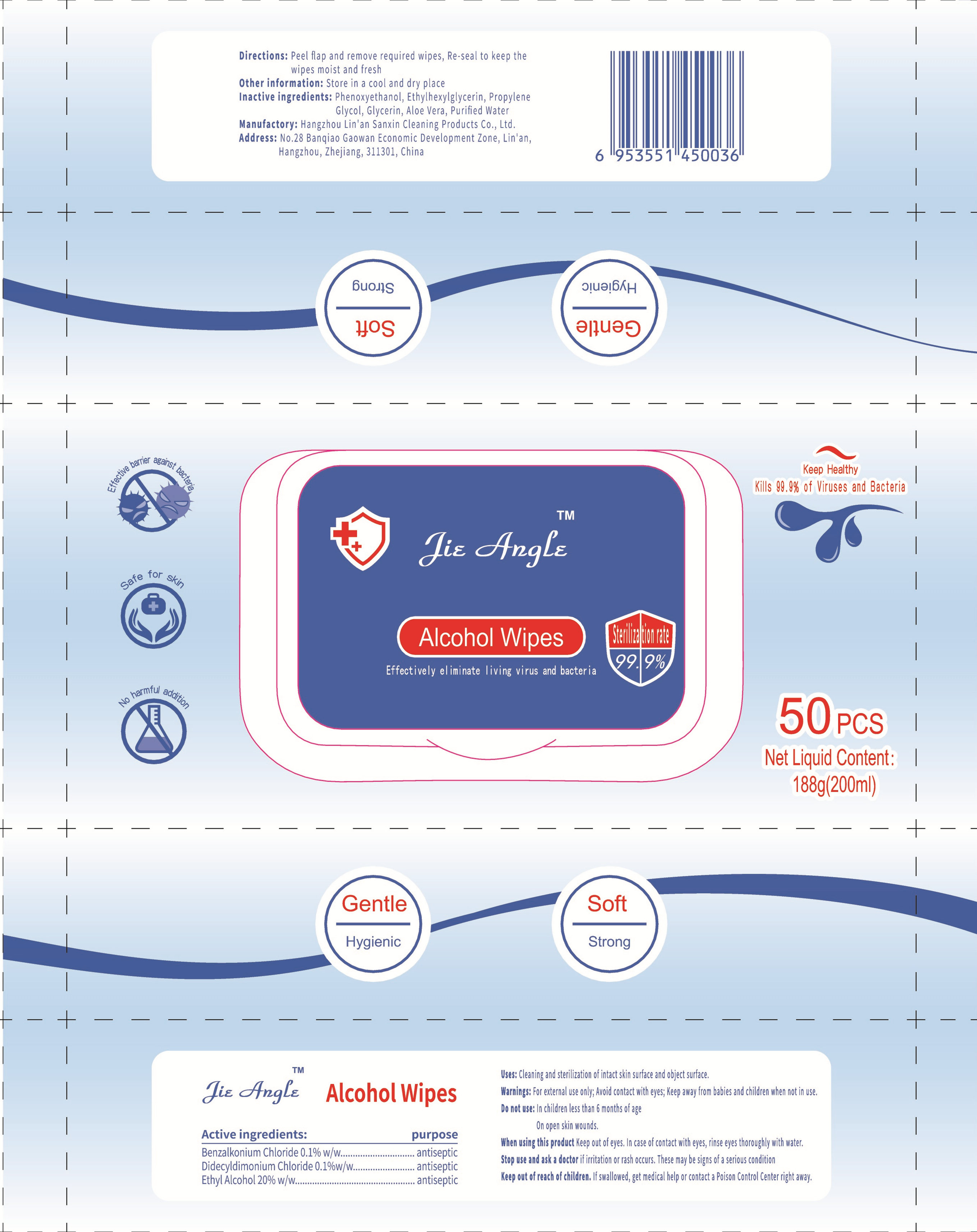 DRUG LABEL: Alcohol Wipes
NDC: 54279-001 | Form: CLOTH
Manufacturer: Hangzhou Lin'an Sanxin Cleaning Products Co.,Ltd.
Category: otc | Type: HUMAN OTC DRUG LABEL
Date: 20200511

ACTIVE INGREDIENTS: BENZALKONIUM CHLORIDE 0.188 g/50 1; DIDECYLDIMONIUM CHLORIDE 0.188 g/50 1; ALCOHOL 40 mL/50 1
INACTIVE INGREDIENTS: PHENOXYETHANOL; ETHYLHEXYLGLYCERIN; WATER; GLYCERIN; ALOE VERA LEAF; PROPYLENE GLYCOL

DOSAGE AND ADMINISTRATION

Store in a cool and dry place

INACTIVE INGREDIENT

Phenoxyethanol，Ethylhexylglycerin，Propylene Glycol，Glycerin，Aloe Vera，Purified Water

INDICATIONS AND USAGE

Peel flap and remove required wipes,wipe back and forth

ACTIVE INGREDIENT

Benzalkonium Chloride

Didecyldimonium Chloride

Ethyl Alcohol

keep out of reach of children

PURPOSE

Disinfection
Sterilization
No Rinseing

WARNINGS

For external use only; Avoid contact with eyes; Keep away from babies and cilren when not in use.